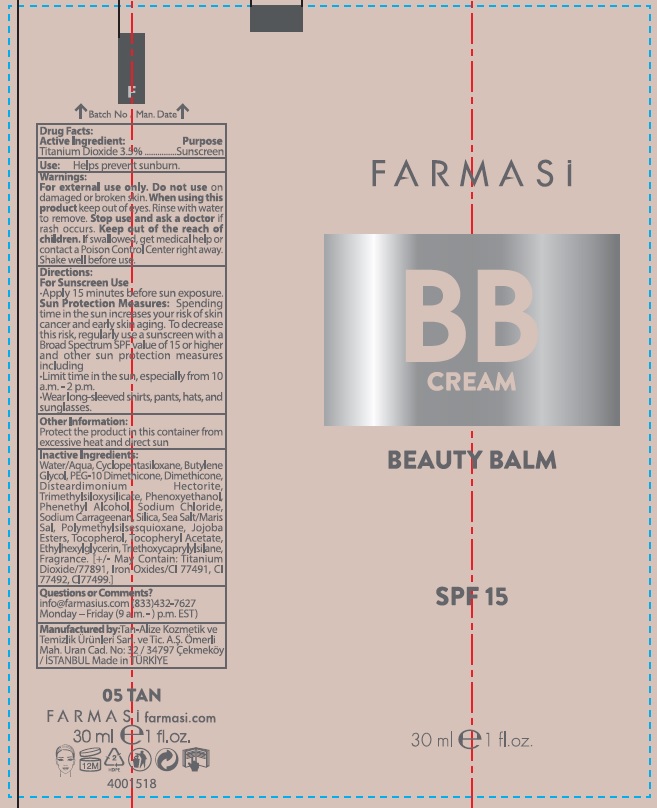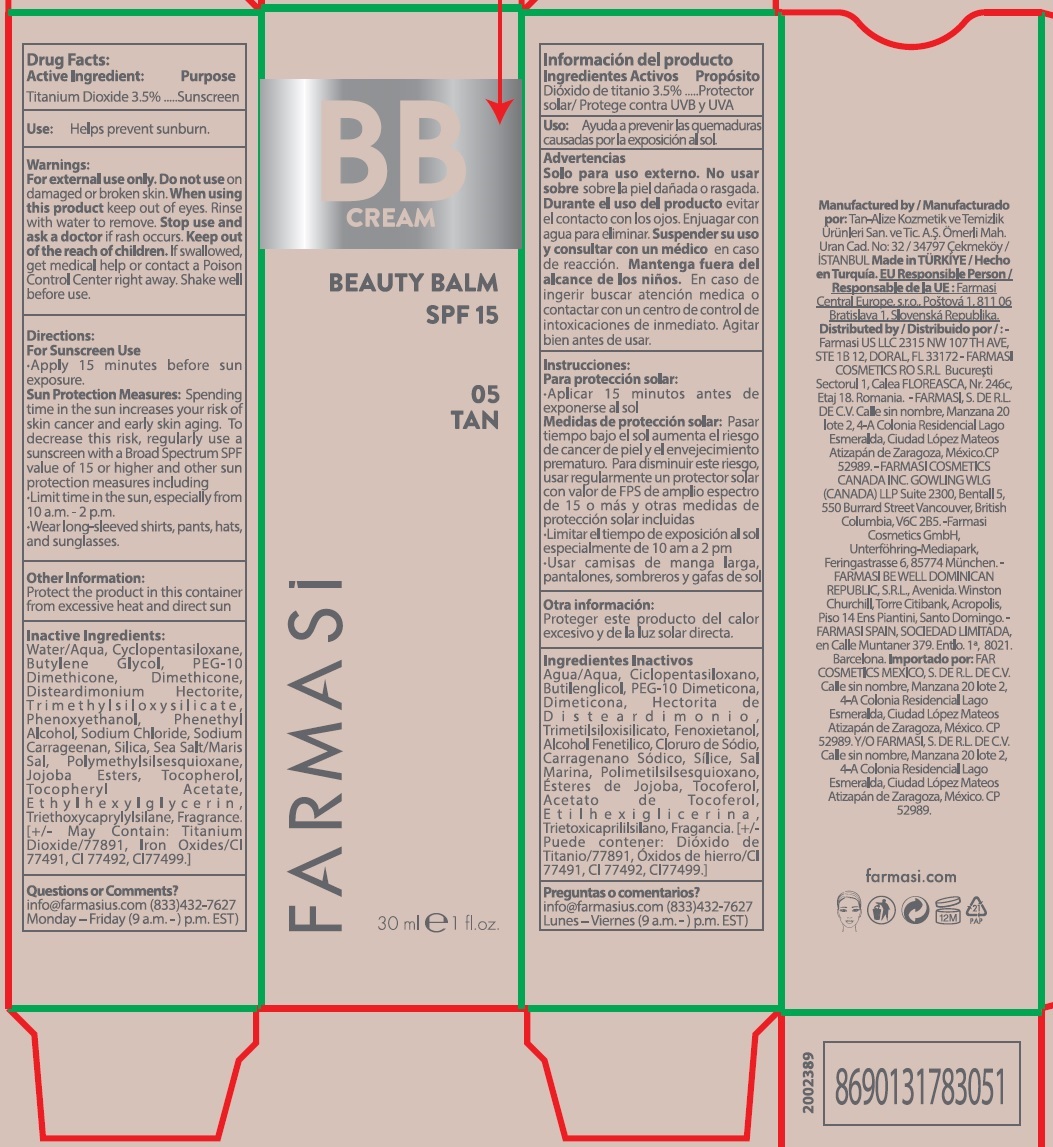 DRUG LABEL: Farmasi BB Beauty Balm Cream SPF 15- 05 Tan
NDC: 74690-044 | Form: CREAM
Manufacturer: Farmasi US LLC
Category: otc | Type: HUMAN OTC DRUG LABEL
Date: 20231105

ACTIVE INGREDIENTS: TITANIUM DIOXIDE 35 mg/1 mL
INACTIVE INGREDIENTS: WATER; CYCLOMETHICONE 5; BUTYLENE GLYCOL; DIMETHICONE; DISTEARDIMONIUM HECTORITE; PHENOXYETHANOL; PHENYLETHYL ALCOHOL; SODIUM CHLORIDE; CARRAGEENAN SODIUM; SILICON DIOXIDE; POLYMETHYLSILSESQUIOXANE (4.5 MICRONS); TOCOPHEROL; .ALPHA.-TOCOPHEROL ACETATE; ETHYLHEXYLGLYCERIN; TRIETHOXYCAPRYLYLSILANE

Farmasi BB Beauty Balm Cream SPF 15- 05 Tan

Active Ingredient:

Titanium Dioxide 3.5%

Purpose

Sunscreen

Use:

Helps prevent sunburn.

Warnings:

For external use only.

Do not use

- on damaged or broken skin.

When using this product

keep out of eyes. Rinse with water to remove.

Stop use and ask a doctor

if rash occurs.

Keep out of the reach of children.

If swallowed, get medical help or contact a Poison Control Center right away. Shake well before use.

Directions:

· Apply 15 minutes before sun exposure. · Spending time in the sun increases your risk of skin cancer and early skin aging. To decrease this risk, regularly use a sunscreen with a Broad Spectrum SPF value of 15 or higher and other sun protection measures including · Limit time in the sun, especially from 10 a.m. - 2 p.m.· Wear long-sleeved shirts, pants, hats, and sunglasses. For Sunscreen Use Sun Protection Measures:

Other Information:

protect the product in this container from excessive heat and direct sun

Inactive Ingredients:

Water/Aqua, Cyclopentasiloxane, Butylene Glycol, PEG-10 Dimethicone, Dimethicone, Disteardimonium Hectorite, Tr i m e t h y l s i l o x y s i l i c a t e , Phenoxyethanol, Phenethyl Alcohol, Sodium Chloride, Sodium Carrageenan, Silica, Sea Salt/Maris Sal, Polymethylsilsesquioxane, Jojoba Esters, Tocopherol, Tocopheryl Acetate, E t h y l h e x y l g l y c e r i n , Triethoxycaprylylsilane, Fragrance. [+/- May Contain: Titanium Dioxide/77891, Iron Oxides/CI 77491, CI 77492, CI77499.]

Questions or Comments?

info@farmasius.com (833)432-7627 Monday – Friday (9 a.m. -) p.m. EST)